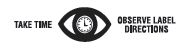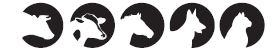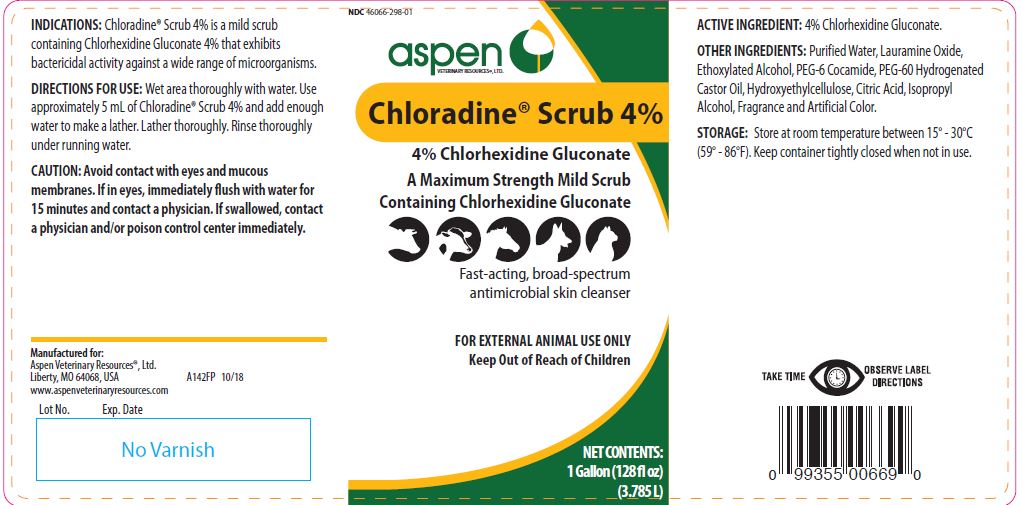 DRUG LABEL: Chloradine Scrub
NDC: 46066-298 | Form: LIQUID
Manufacturer: Aspen Veterinary
Category: animal | Type: OTC ANIMAL DRUG LABEL
Date: 20221114

ACTIVE INGREDIENTS: CHLORHEXIDINE GLUCONATE 214.5 g/1 L

Chloradine® Scrub 4%

A Maximum Strength Mild Scrub Containing Chlorhexidine Gluconate

Fast-acting, broad-spectrum antimicrobial skin cleanser

KEEP OUT OF REACH OF CHILDREN

FOR EXTERNAL ANIMAL USE ONLY
Keep Out of Reach of Children

NET CONTENTS:

1 Gallon (128 fl oz) (3.785 L)

INDICATIONS:

Chloradine® Scrub 4% is a mild scrub containing Chlorhexidine Gluconate 4% that exhibits bactericidal activity against a wide range of microorganisms.

DIRECTIONS FOR USE:

Wet area thoroughly with water. Use approximately 5 mL of Chloradine® Scrub 4% and add enough water to make a lather. Lather thoroughly. Rinse thoroughly under running water.

CAUTION:

Avoid contact with eyes and mucous membranes. If in eyes, immediately flush with water for 15 minutes and contact a physician. If swallowed, contact a physician and/or poison control center immediately.

ACTIVE INGREDIENT:

4% Chlorhexidine Gluconate.

OTHER INGREDIENTS:

Purified Water, Lauramine Oxide, Ethoxylated Alcohol, PEG-6 Cocamide, PEG-60 Hydrogenated Castor Oil, Hydroxyethylcellulose, Citric Acid, Isopropyl Alcohol, Fragrance and Artificial Color.

STORAGE:

Store at room temperature between 15° - 30°C (59° - 86°F). Keep container tightly closed when not in use.

INFORMATION FOR OWNERS/CAREGIVERS

Manufactured for:
Aspen Veterinary Resources®, Ltd.
Liberty, MO 64068, USA A142FP 10/18
www.aspenveterinaryresources.com